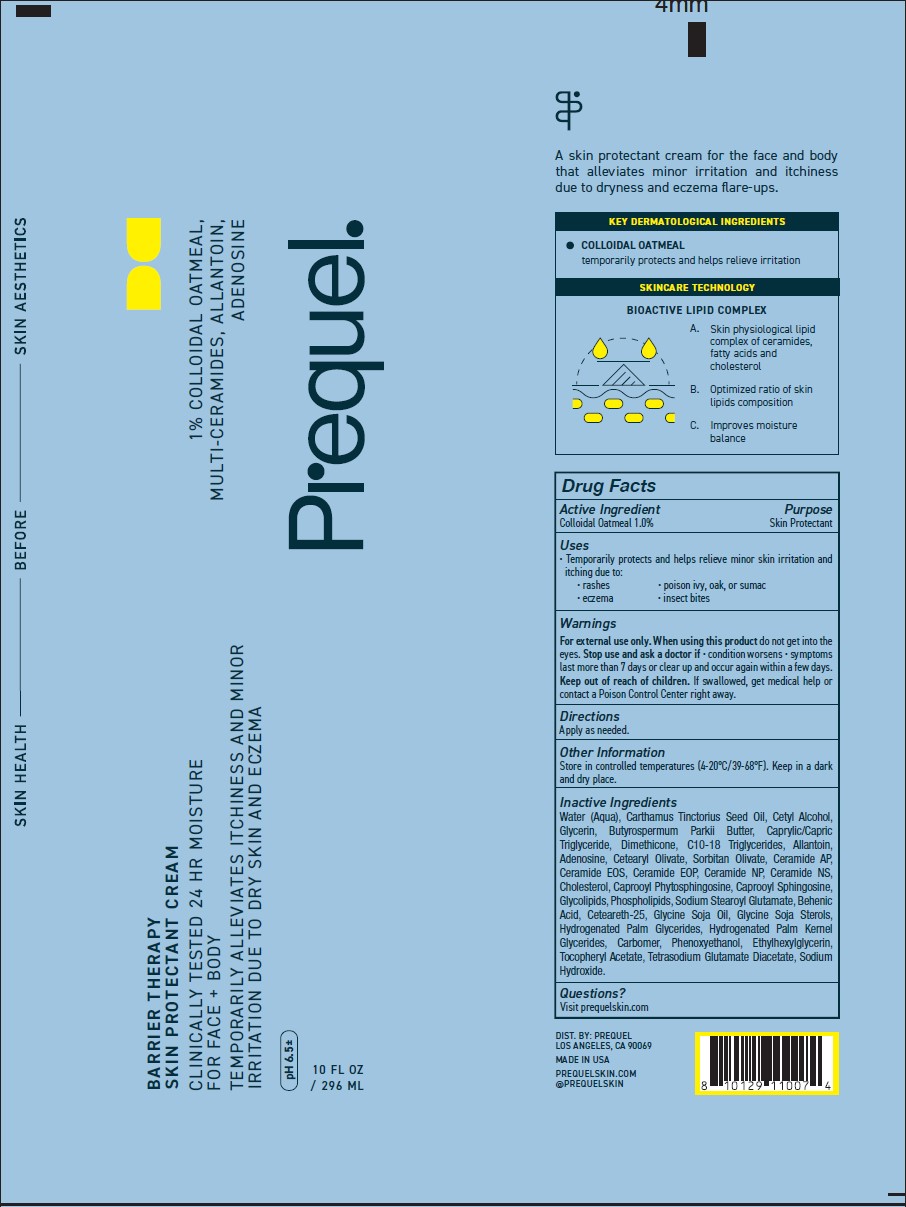 DRUG LABEL: Prequel Barrier Cream
NDC: 82800-009 | Form: CREAM
Manufacturer: The Center Brands, LLC
Category: otc | Type: HUMAN OTC DRUG LABEL
Date: 20251031

ACTIVE INGREDIENTS: OATMEAL 1 g/100 g
INACTIVE INGREDIENTS: CETEARETH-25; SOY STEROL; CAPROOYL PHYTOSPHINGOSINE; C10-18 TRIGLYCERIDES; ALLANTOIN; ADENOSINE; CERAMIDE AP; CERAMIDE EOS; TETRASODIUM GLUTAMATE DIACETATE; OMEGA-3 FATTY ACIDS; CERAMIDE NP; GLYCERIN; SHEA BUTTER; SODIUM STEAROYL GLUTAMATE; CETYL ALCOHOL; DIMETHICONE; PHENOXYETHANOL; .ALPHA.-TOCOPHEROL ACETATE; SORBITAN OLIVATE; N-HEXANOYLSPHINGOSINE; CETEARYL OLIVATE; CERAMIDE 2; WATER; CERAMIDE 1; CHOLESTEROL; BEHENIC ACID; SOYBEAN OIL; MEDIUM-CHAIN TRIGLYCERIDES; SAFFLOWER OIL; CARBOMER HOMOPOLYMER, UNSPECIFIED TYPE; HYDROGENATED PALM GLYCERIDES; HYDROGENATED PALM KERNEL GLYCERIDES; ETHYLHEXYLGLYCERIN; SODIUM HYDROXIDE

THE05-Barrier Therapy Skin Protectant Cream

Purpose

Skin Protectant

Active Ingredients

Colloidal Oatmeal 1.00%

Uses

Temporarily protects and helps releive minor skin irritation and itching due:

rashes

eczema

poison ivy, oak, or sumac

insect biktes

Warnings

Fox external use only.

When using this product do not get into eyes

Stop use and ask a doctor if

condition worsens
symptoms last more than 7 days or clear up and occur again within a few days

Keep out of reach of children. If swallowed, get medical help or contact a Poison Control Center right away.

Directions

Apply as needed.

Inactive Ingredients

Water (Aqua), Carthamus Tinctorius Seed Oil, Cetyl Alcohol, Glycerin, Butyrospermum Parkii Butter, Caprylic/Capric Triglyceride, Dimethicone, C10-18 Trigylcerides, Allantoin, Adenosine, Cetearyl Olivate, Sorbitan Olivate, Ceramide AP, Ceramide EOS, Ceramide EOP, Ceramide NP, Ceramide NS, Cholesterol, Caprooyl Phytosphingosine, Caprooyl Sphingosine, Glycolipids, Phospholipids, Sodium Stearoyl Glutamate, Behenic Acide, Ceteareth-25, Glycine Soja Sterols, Hydrogenated Palm Glycerides, Hydrogenated Palm Kernel Glycerides, Carbomer, Phenoxyethanol, Ethylhexylglycerin, Tocopheryl Acetate, Tetrasodium Glutamate Diacetate, Sodium Hydroxide

Questions?

Visit prequelskin.com